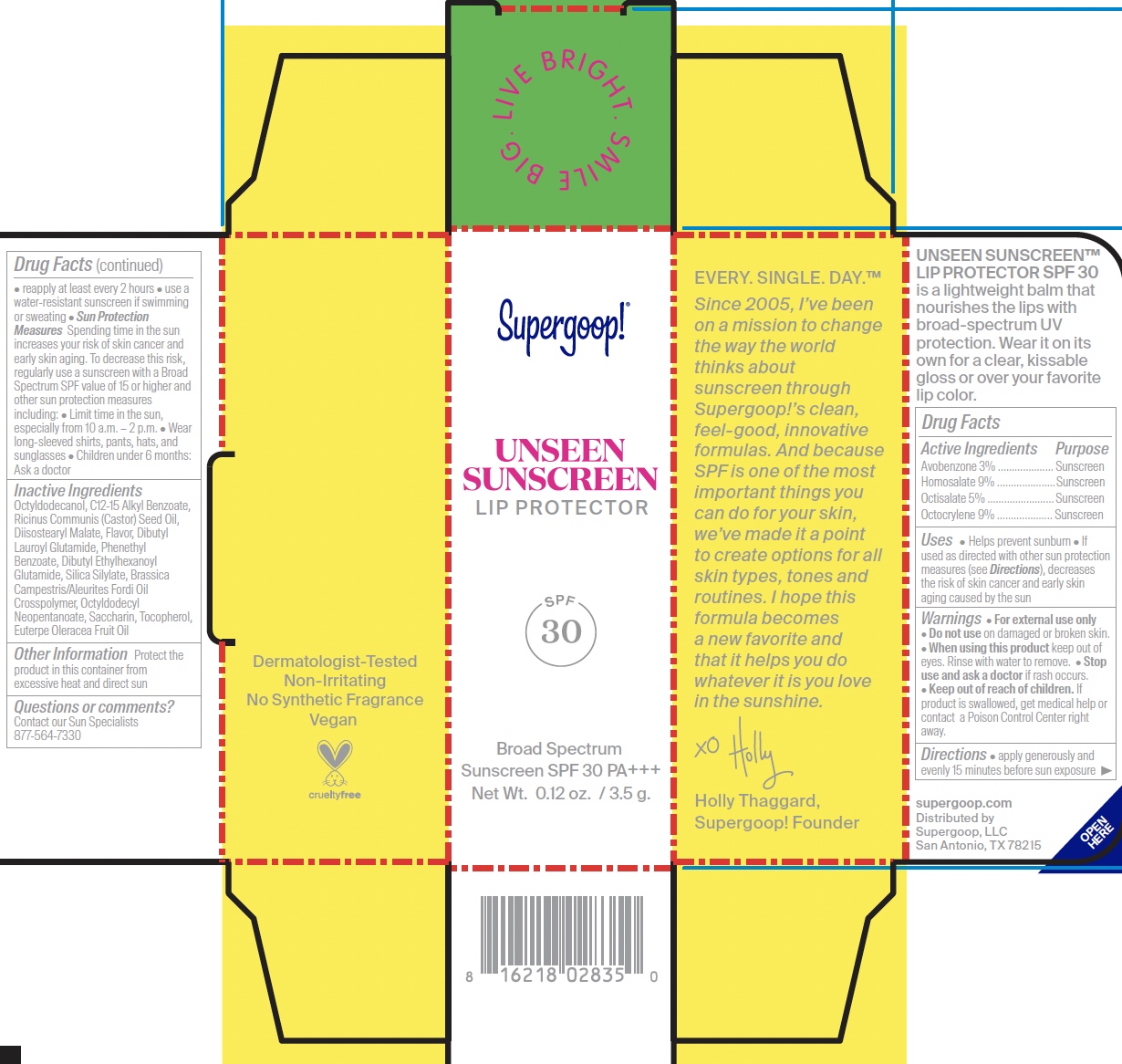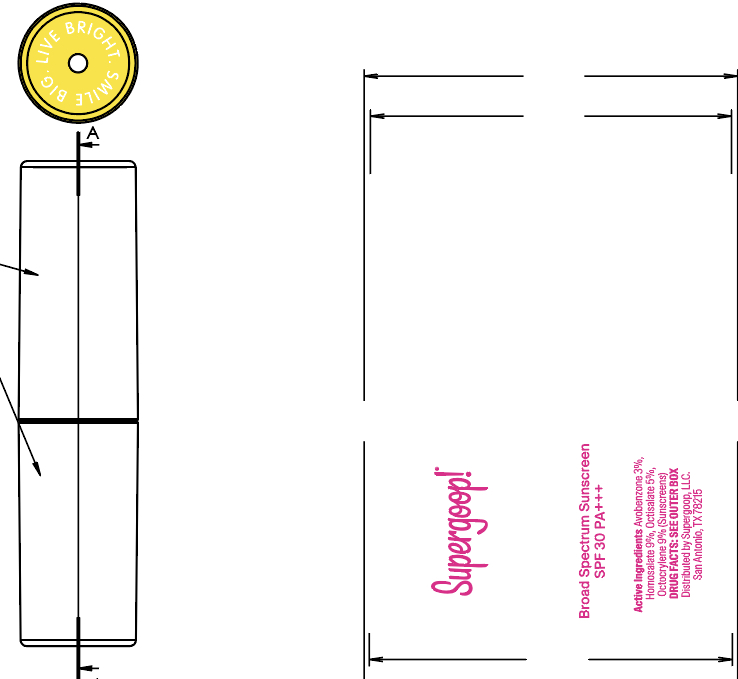 DRUG LABEL: Unseen Sunscreen Lip Protector SPF 30
NDC: 75936-638 | Form: STICK
Manufacturer: Supergoop, LLC
Category: otc | Type: HUMAN OTC DRUG LABEL
Date: 20240227

ACTIVE INGREDIENTS: AVOBENZONE 3 g/100 mL; OCTISALATE 5 g/100 mL; HOMOSALATE 9 g/100 mL; OCTOCRYLENE 9 g/100 mL
INACTIVE INGREDIENTS: SILICA DIMETHYL SILYLATE; OCTYLDODECYL NEOPENTANOATE; OCTYLDODECANOL; BRASSICA RAPA VAR. RAPA OIL; DIBUTYL ETHYLHEXANOYL GLUTAMIDE; DIISOSTEARYL MALATE; RICINUS COMMUNIS SEED; EUTERPE OLERACEA WHOLE; DIBUTYL LAUROYL GLUTAMIDE; PHENETHYL BENZOATE; SACCHARIN; TOCOPHEROL; ALKYL (C12-15) BENZOATE; DRYOBALANOPS AROMATICA WHOLE

Unseen Sunscreen Lip Protector

ACTIVE INGREDIENT

Active Ingredients: Avobenzone 3% Homosalate 9% Octisalate 5% Octocrylene 9%

INACTIVE INGREDIENT

Inactive Ingredients: Octyldodecanol, C12-15 Alkyl Benzoate, Ricinus Communis (Castor) Seed Oil, Diisostearyl Malate, Flavor, Dibutyl Lauroyl Glutamide, Phenethyl Benzoate, Dibutyl Ethylhexanoyl Glutamide, Silica Silylate, Brassica Campestris/Aleurites Fordi Oil Crosspolymer, Octyldodecyl Neopentanoate, Saccharin, Tocopherol, Euterpe Oleracea Fruit Oil

PURPOSE

Helps prevent sunburn

If used as directed with other sun protection measures (see Directions), decreases the risk of skin cancer and early skin aging caused by the sun

Keep out of reach of children. If product is swallowed, get medical help, or contact a poison control center right away.

WARNINGS

For External use only

Do not use on damaged or broken skin

When using this product, keep out of eyes. Rinse with water to remove

Stop use and ask a doctor if rash occurs

Directions

Apply generously and evenly 15 minutes before sun exposure

Reapply at least every 2 hours

Use a water resistant sunscreen if swimming or sweating

Sun Protection Measures: Spending time in the sun increases your risk of skin cancer and early skin aging. To decrease this risk, regularly use a sunscreen with a Broad Spectrum SPF value of 15 or higher and other sun protection measures including:

Limit time in the sun, especially from 10 a.m.- 2 p.m.

Wear long-sleeved shirts, pants, hats, and sunglasses

Children under 6 months: Ask a doctor

PACKAGE LABEL

Unseen Sunscreen Lip Protector SPF 30

Secondary Packaging

Primary Packaging